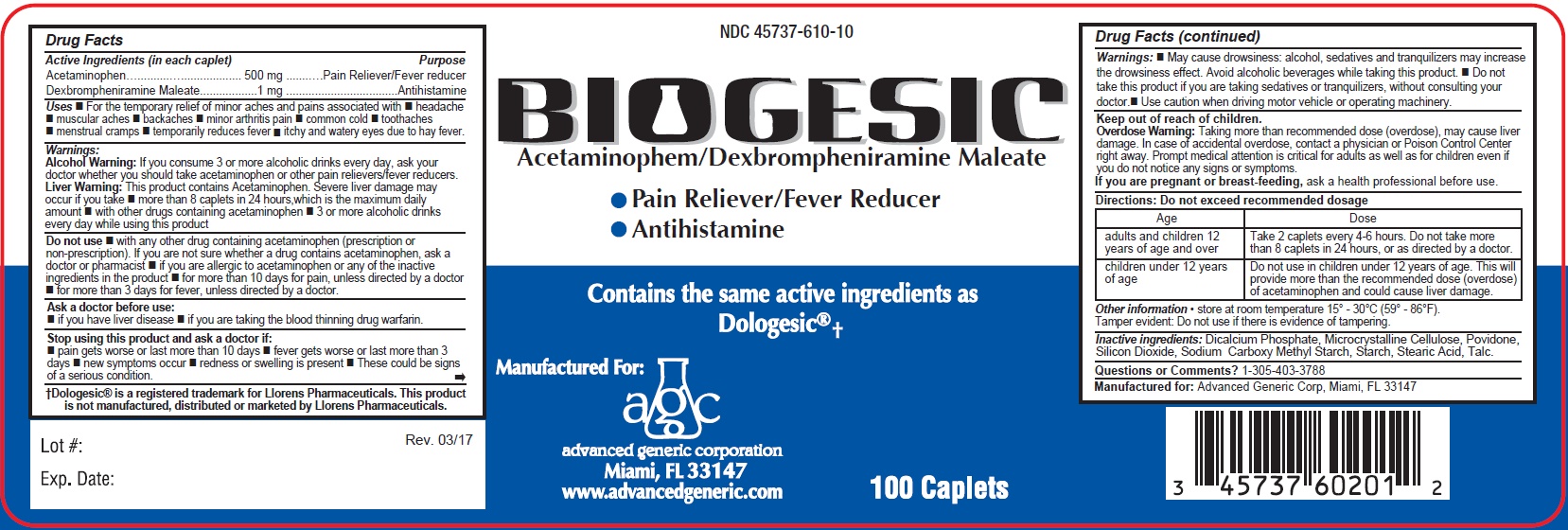 DRUG LABEL: Biogesic
NDC: 45737-610 | Form: TABLET
Manufacturer: Advanced Generic Corporation
Category: otc | Type: HUMAN OTC DRUG LABEL
Date: 20241220

ACTIVE INGREDIENTS: ACETAMINOPHEN 500 mg/1 1; DEXBROMPHENIRAMINE MALEATE 1 mg/1 1
INACTIVE INGREDIENTS: ANHYDROUS DIBASIC CALCIUM PHOSPHATE; MICROCRYSTALLINE CELLULOSE; POVIDONE; SILICON DIOXIDE; CARBOXYMETHYLCELLULOSE SODIUM; STARCH, CORN; STEARIC ACID; TALC

AGC-Biogesic Tab 610

Active ingredients (in each caplet) Purpose

Acetaminophen 500 mg Pain Reliever/Fever Reducer

Dexbrompheniramine maleate 1 mg Antihistamine

Purpose

Antihistamine

Nasal Decongestant

Warnings:
Alcohol Warning:If you consume 3 or more alcoholic drinks every day, ask your
doctor whether you should take acetaminophen or other pain relievers/fever reducers.
Liver Warning:This product contains Acetaminophen. Severe liver damage may
occur if you take

- more than 8 caplets in 24 hours,which is the maximum daily amount
- with other drugs containing acetaminophen
- 3 or more alcoholic drinks every day while using this product

Do not use

- with any other drug containing acetaminophen (prescription or non-prescription). If you are not sure whether a drug contains acetaminophen, ask a doctor or pharmacist
- if you are allergic to acetaminophen or any of the inactive ingredients in the product
- for more than 10 days for pain, unless directed by a doctor
- for more than 3 days for fever, unless directed by a doctor.

Ask a doctor before use:

- if you have liver disease
- if you are taking the blood thinning drug warfarin.

Stop using this product and ask a doctor if:

- pain gets worse or last more than 10 days
- fever gets worse or last more than 3 days
- new symptoms occur n redness or swelling is present
- These could be signs of a serious condition.

Warnings:

- May cause drowsiness: alcohol, sedatives and tranquilizers may increase the drowsiness effect. Avoid alcoholic beverages while taking this product.
- Do not take this product if you are taking sedatives or tranquilizers, without consulting your doctor.
- Use caution when driving motor vehicle or operating machinery.

Overdose Warning:Taking more than recommended dose (overdose), may cause liver
damage. In case of accidental overdose, contact a physician or Poison Control Center
right away. Prompt medical attention is critical for adults as well as for children even if
you do not notice any signs or symptoms.

Keep out of reach of children.

Overdose Warning: Taking more than recommended dose (overdose), may cause liver
damage. In case of accidental overdose, contact a physician or Poison Control Center
right away. Prompt medical attention is critical for adults as well as for children even if
you do not notice any signs or symptoms.

PREGNANCY OR BREAST FEEDING

If pregnant or breast-feeding, ask a Health Professional before use.

Directions: Do not exceed recommended dosage

adults and children 12 years of age and over | Take 2 caplets every 4-6 hours. Do not take more; than 8 caplets in 24 hours, or as directed by a doctor.
children under 12 years of age | Do not use in children under 12 years of age.; This will provide more than the recommended dose (overdose); of acetaminophen and could cause liver damage.

Uses

- For the temporary relief of minor aches and pains associated with
- headache
- muscular aches
- backaches
- minor arthiritis pain
- common cold
- toothaches
- mentrual cramps
- temporarily reduces fever
- itchy and watery eyes due to hay fever

INACTIVE INGREDIENT

Inactive ingredients: dicalcium phasphate, microcrystalline cellulose, povidone, silicon dioxide, sodium carboxymethyl starch, starch, stearic acid, talc.

Questions or comments?

1-305-403-3788